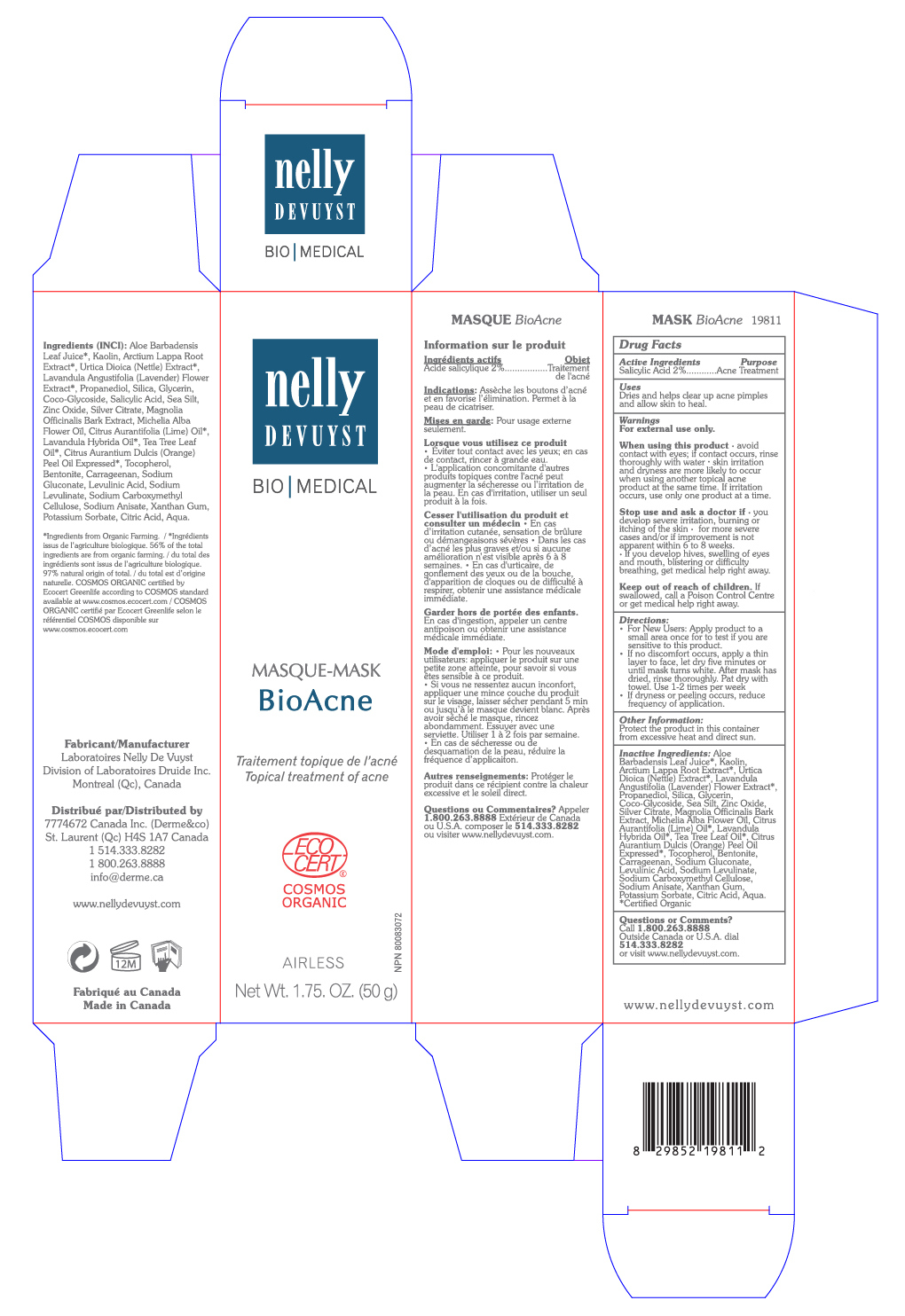 DRUG LABEL: NELLY DEVUYST MASK BIOACNE
NDC: 71447-005 | Form: CREAM
Manufacturer: LABORATOIRES DRUIDE INC
Category: otc | Type: HUMAN OTC DRUG LABEL
Date: 20210101

ACTIVE INGREDIENTS: SALICYLIC ACID 2 g/100 g
INACTIVE INGREDIENTS: ZINC OXIDE; LAVANDIN OIL; TEA TREE OIL; MICHELIA ALBA LEAF OIL; CITRUS AURANTIIFOLIA FRUIT OIL; ALOE VERA LEAF; KAOLIN; CITRUS AURANTIUM FRUIT OIL; BENTONITE; CARBOXYMETHYLCELLULOSE SODIUM; XANTHAN GUM; CITRIC ACID MONOHYDRATE; WATER; SEA SALT; SILVER CITRATE; MAGNOLIA OFFICINALIS BARK; TOCOPHEROL; CARRAGEENAN; SODIUM GLUCONATE; LEVULINIC ACID; SODIUM LEVULINATE; URTICA DIOICA LEAF; LAVANDULA ANGUSTIFOLIA FLOWER; PROPANEDIOL; ARCTIUM LAPPA ROOT OIL; GLYCERIN; POTASSIUM SORBATE; COCO GLUCOSIDE; SODIUM ANISATE; SILICON DIOXIDE

NELLY DEVUYST MASK BIOACNE 50 g

Active Ingredients

Salicylic Acid 2%

Purpose

Acne Treatment

Uses

Dries and helps clear up acne pimples, and allows skin to heal.

Warnings

For external use only.

When using this product

▪ avoid contact with eyes. If contact occurs, rinse thoroughly with water ▪ Skin irritation and dryness are more likely to occur when using another topical acne product at the same time. If irritation occurs, use only one product at a time.

and ask a doctor if

▪ you develop severe irritation, burning or itching of the skin ▪ for more severe cases and or if improvement is not apparent within 6 to 8 weeks ▪ If you develop hives, swelling of eyes and mouth, blistering or difficulty breathing, get medical help right away.

Keep out of reach of children.

If swallowed, get medical help or contact a Poison Control Center right away.

Directions

▪ For new users: apply product to a small area once to test if you are sensitive to this product.

▪ If no discomfort occurs, apply a thin layer to face, let dry five minutes or until mask turns white. After mask has dried, rinse thoroughly. Pat dry with towel. Use 1-2 times per week.

▪ If dryness or peeling occurs, reduce frequency of application.

Other Information

Protect the product in this container from excessive heat and direct sun.

Inactive Ingredients

Aloe Barbadensis Leaf Juice*, Kaolin, Arctium Lappa Root Extract*, Urtica Dioica (Nettle) Extract*, Lavandula Angustifolia (Lavender) Flower Extract*, Propanediol, Silica, Glycerin, Coco-Glycoside, Sea Silt, Zinc Oxide, Silver Citrate, Magnolia Officinalis Bark Extract, Michelia Alba Flower Oil, Citrus Aurantifolia (Lime) Oil*, Lavandula Hybrida Oil*, Tea Tree Leaf Oil*, Citrus Aurantium Dulcis (Orange) Peel Oil Expressed*, Tocopherol, Bentonite, Carrageenan, Sodium Gluconate, Levulinic Acid, Sodium Levulinate, Sodium Carboxymethyl Cellulose, Sodium Anisate, Xanthan Gum, Potassium Sorbate, Citric Acid, Aqua.

Certified organic*

Questions or Comments?

+1 800-263-8888

Outside Canada or United States, dial +1 514-333-8282, or visit www.nellydevuyst.com

Distributed By

7774672 Canada Inc (Derme & Co)

4980 Chemin Bois Franc

St. Laurent, QC H4S 1A7

Canada

+1 514-333-8282, +1 800-263-8888

www.nellydevuyst.com

Made in Canada